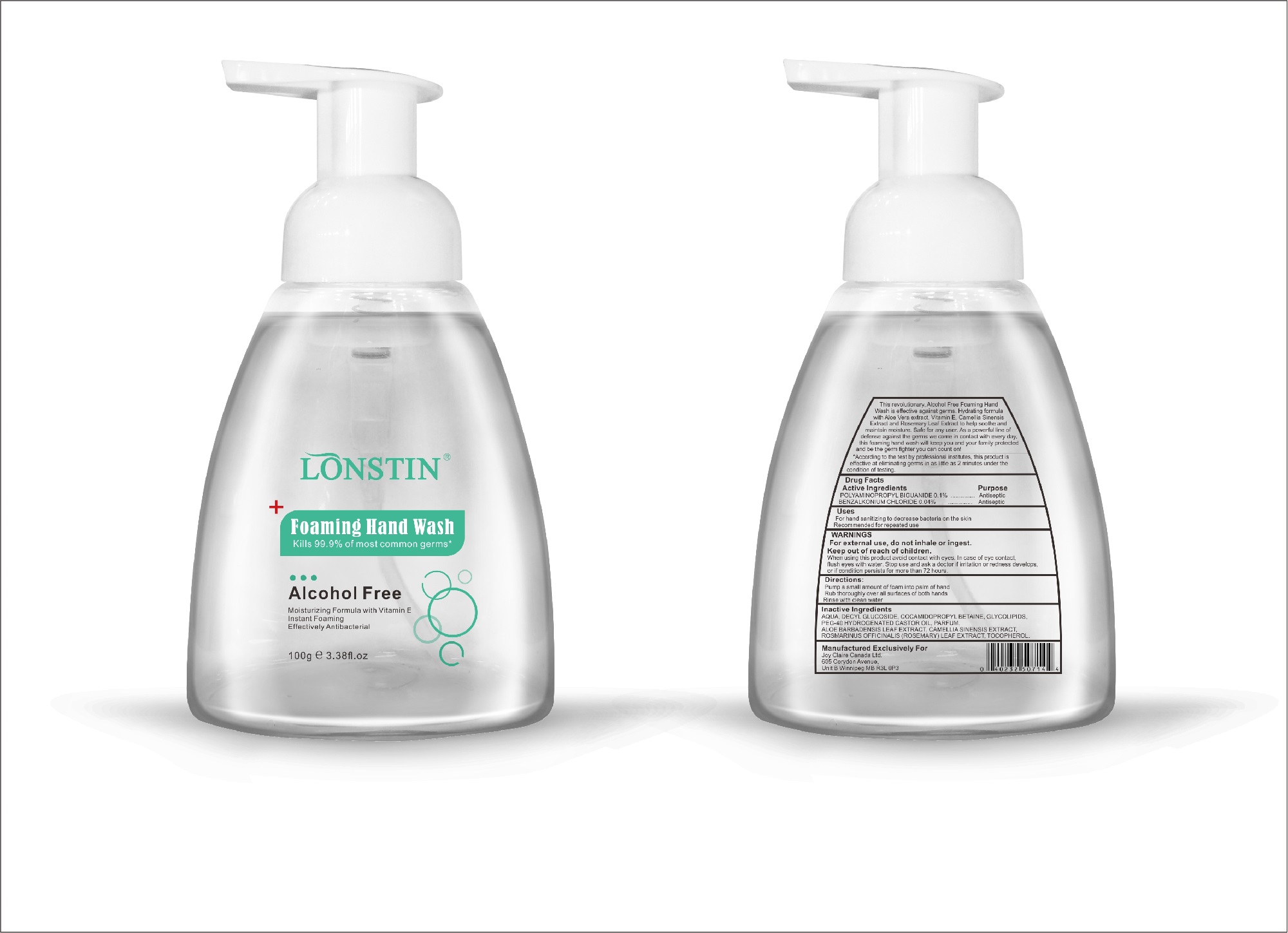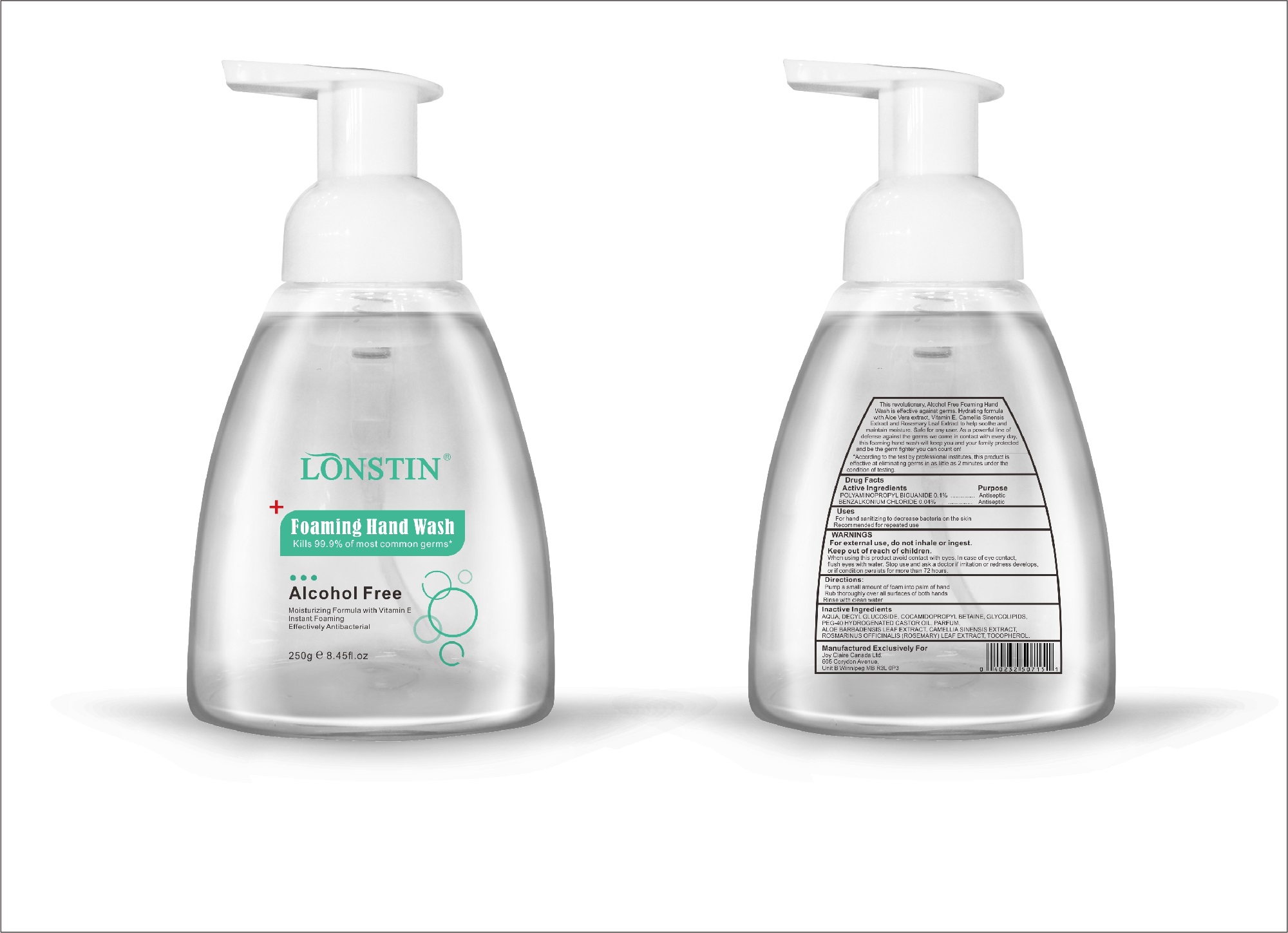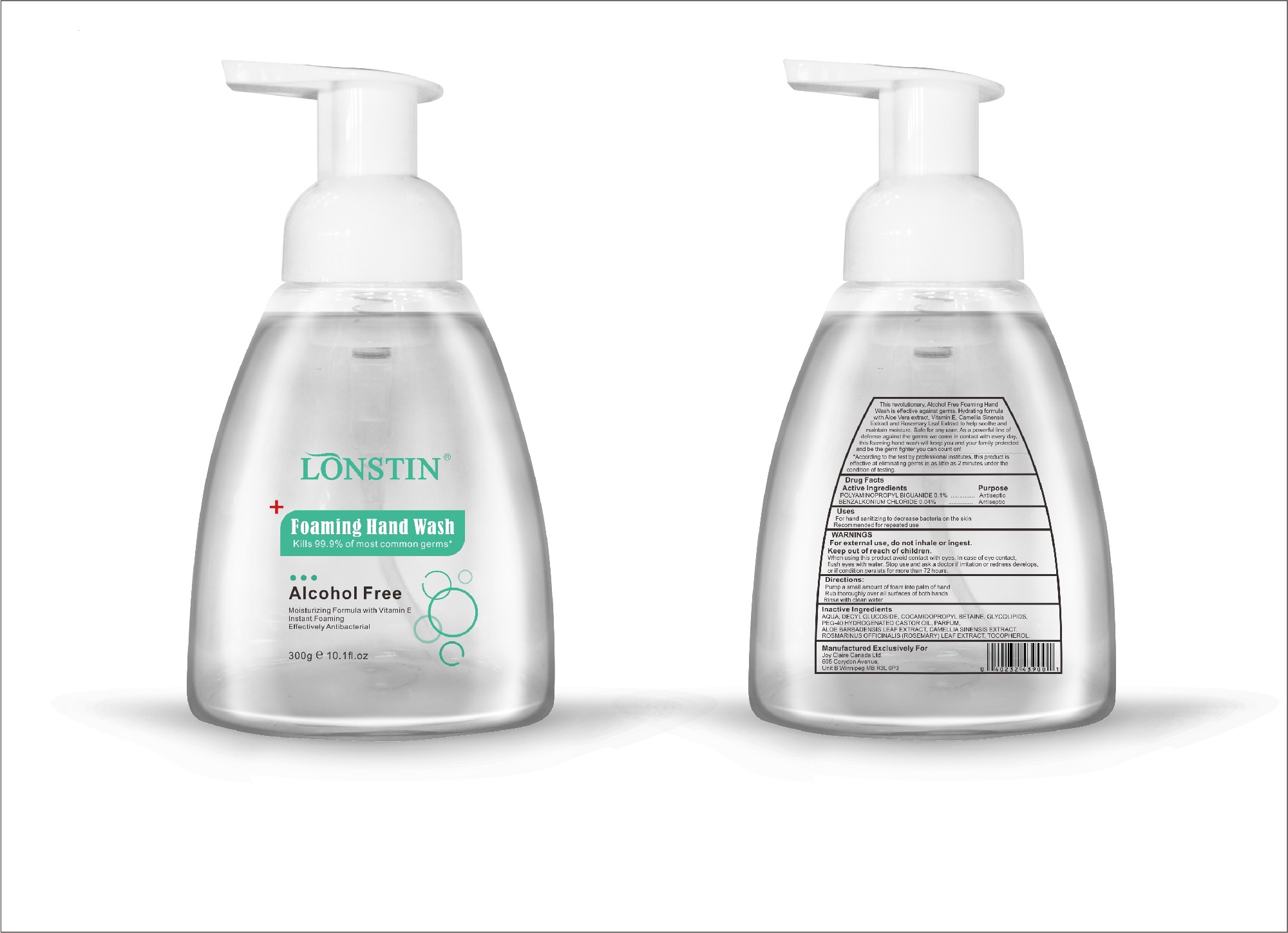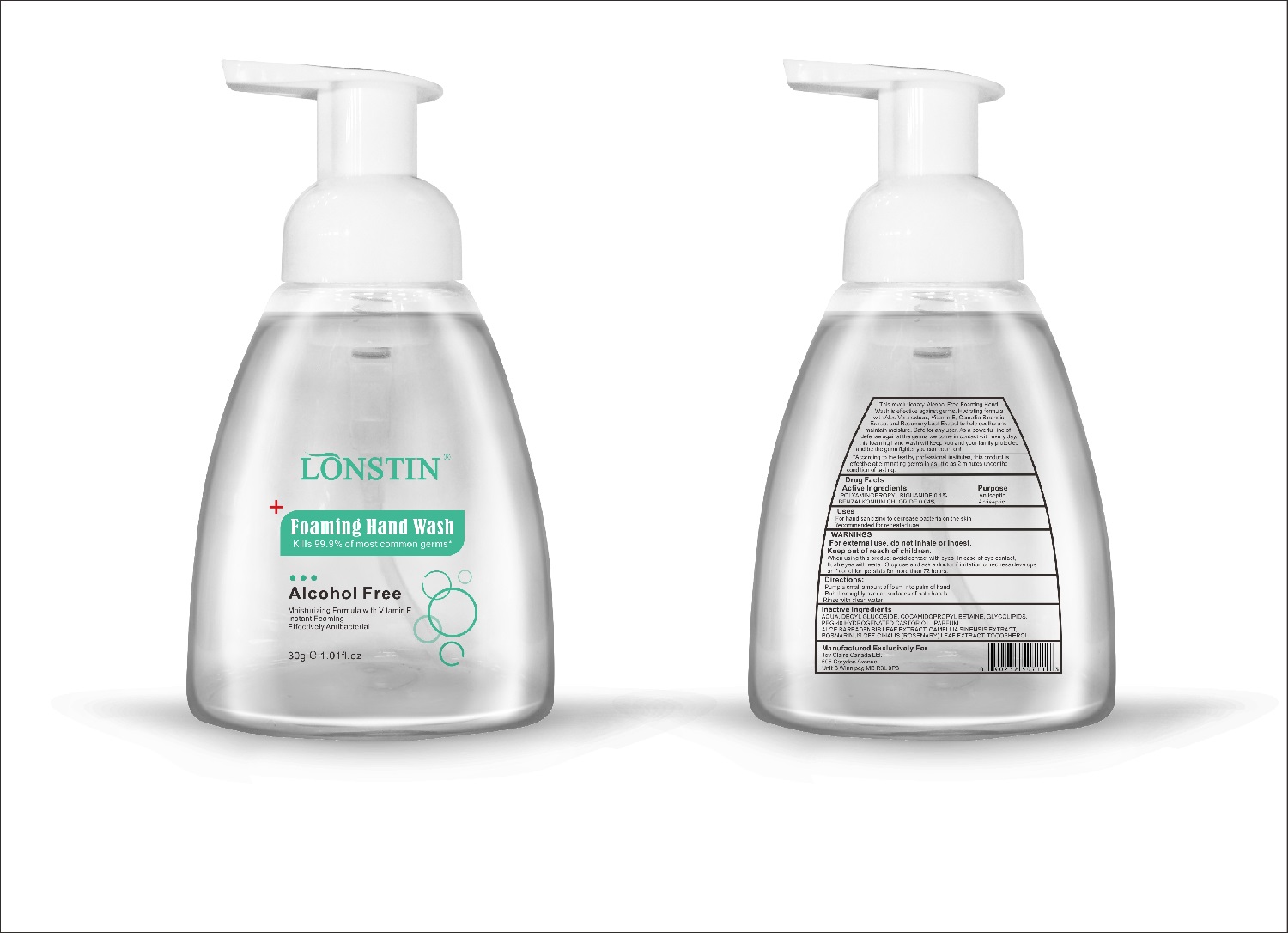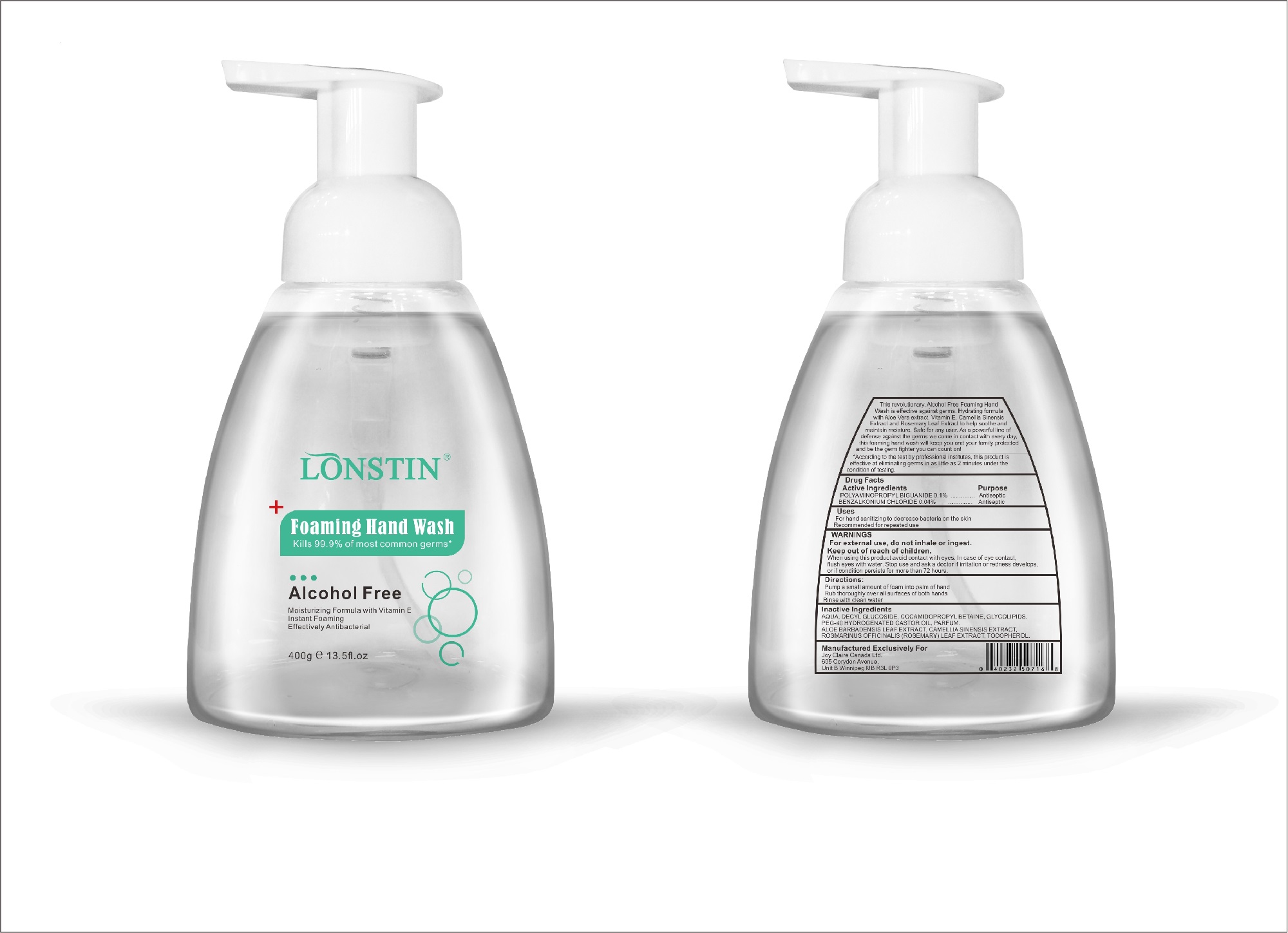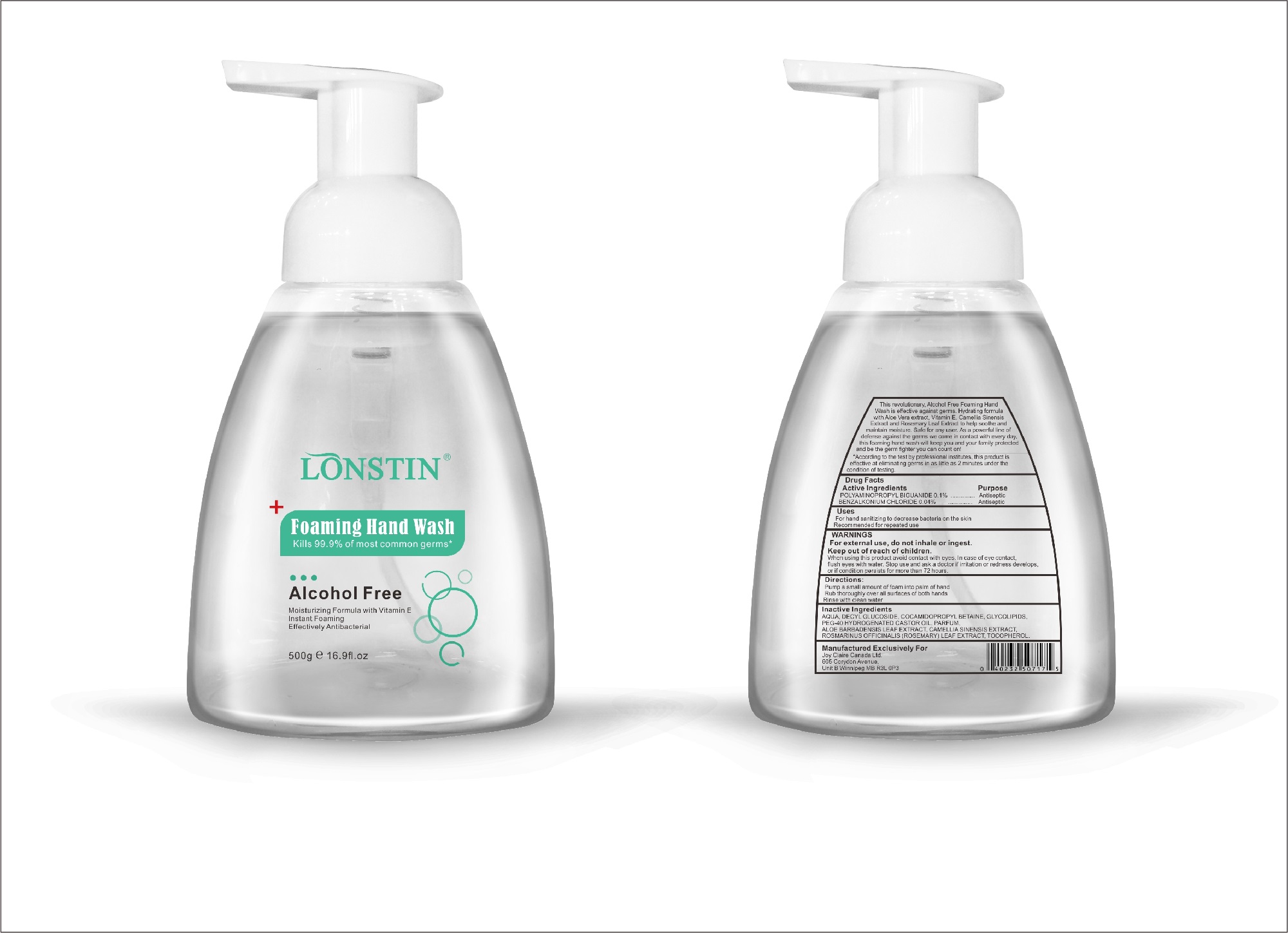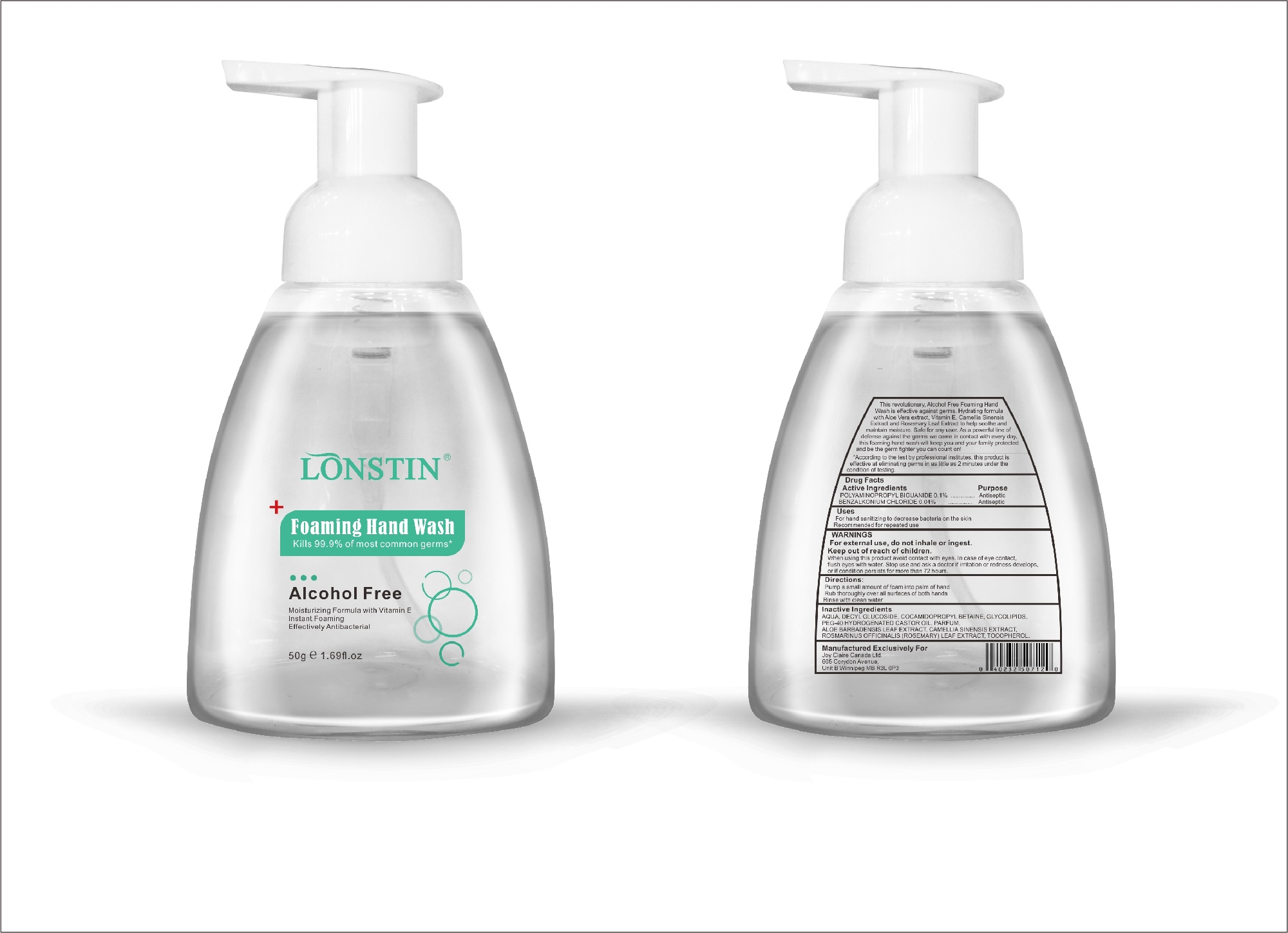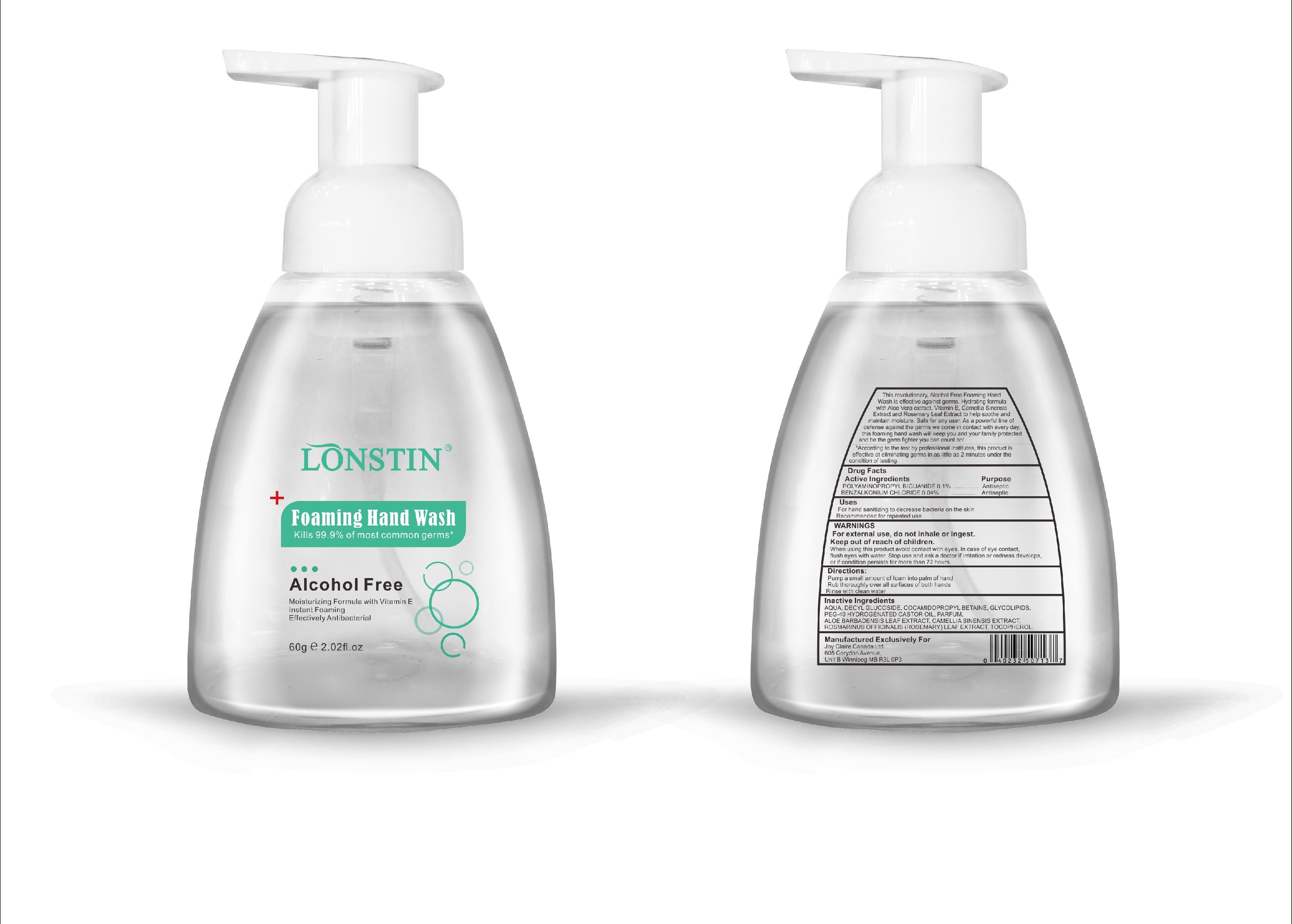 DRUG LABEL: Foaming Hand Wash
NDC: 74743-007 | Form: LIQUID
Manufacturer: Guangzhou Joy Claire Biological Technology   Co., Ltd
Category: otc | Type: HUMAN OTC DRUG LABEL
Date: 20200420

ACTIVE INGREDIENTS: BENZALKONIUM CHLORIDE 0.04 g/100 g; POLYAMINOPROPYL BIGUANIDE 0.1 g/100 g
INACTIVE INGREDIENTS: POLYOXYL 40 HYDROGENATED CASTOR OIL; ALOE; CAMELLIA SINENSIS SEED; ROSEMARY; ALPHA-TOCOPHEROL ACETATE; DECYL GLUCOSIDE; WATER; GLYCOSINE

FOAMING HAND WASH

SUMMARY OF SAFETY AND EFFECTIVENESS

- This revolutionary, Alcohol Free Foaming Hand Wash is effective against germs. Hydrating formula with Aloe Vera extract, Vitamin E. Camellia Sinensis Extract and Rosemary Leaf Extract to help soothe and maintain moisture. Safe for any user. As a powerful line of defense against the germs we come in contact with every day.this foaming hand wash will keep you and your family protected and be the germ fighter you can count on!
- According to the test by professional institutes, this product is effective at eliminating germs in as little as 2 minutes under the condition of testing

Active Ingredient(s)

POLYAMINOPROPYL BIGUANIDE 0.1%

BENZALKONIUM CHLORIDE 0.04%

Purpose

Antiseptic

Uses

For hand sanitizing to decrease bacteria on the skin
Recommended for repeated use

Warnings

For external use, do not inhale or ingest Keep out of reach of children

Keep out of reach of children

Do not use

When using this product avoid contact with eyes.

When using this product keep out of eyes, ears, and mouth. In case of contact with eyes, rinse eyes thoroughly with water.
Stop use and ask a doctor if irritation or rash occurs. These may be signs of a serious condition.
Keep out of reach of children. If swallowed, get medical help or contact a Poison Control Center right away.

Stop use and ask a doctor if irritation or rash occurs. These may be signs of a serious condition.

Directions

Pump a small amount of foam into palm of hand Rub thoroughly over all surfaces of both hands Rinse with clean active

Other information

- Store between 15-30C (59-86F)
- Avoid freezing and excessive heat above 40C (104F)

Inactive ingredients

AQUA, DECYL GLUCOSIDE, COCAMIDOPROPYL BETAINE, GLYCOLIPIDS,
PEG-40 HYDROGENATED CASTOR OIL,PARFUM,
ALOE BARBADENSIS LEAF EXTRACT,CAMELLIA SINENSIS EXTRACT.
ROSMARINUS OFFICINALIS(ROSEMARY)LEAF EXTRACT,TOCOPHEROL.